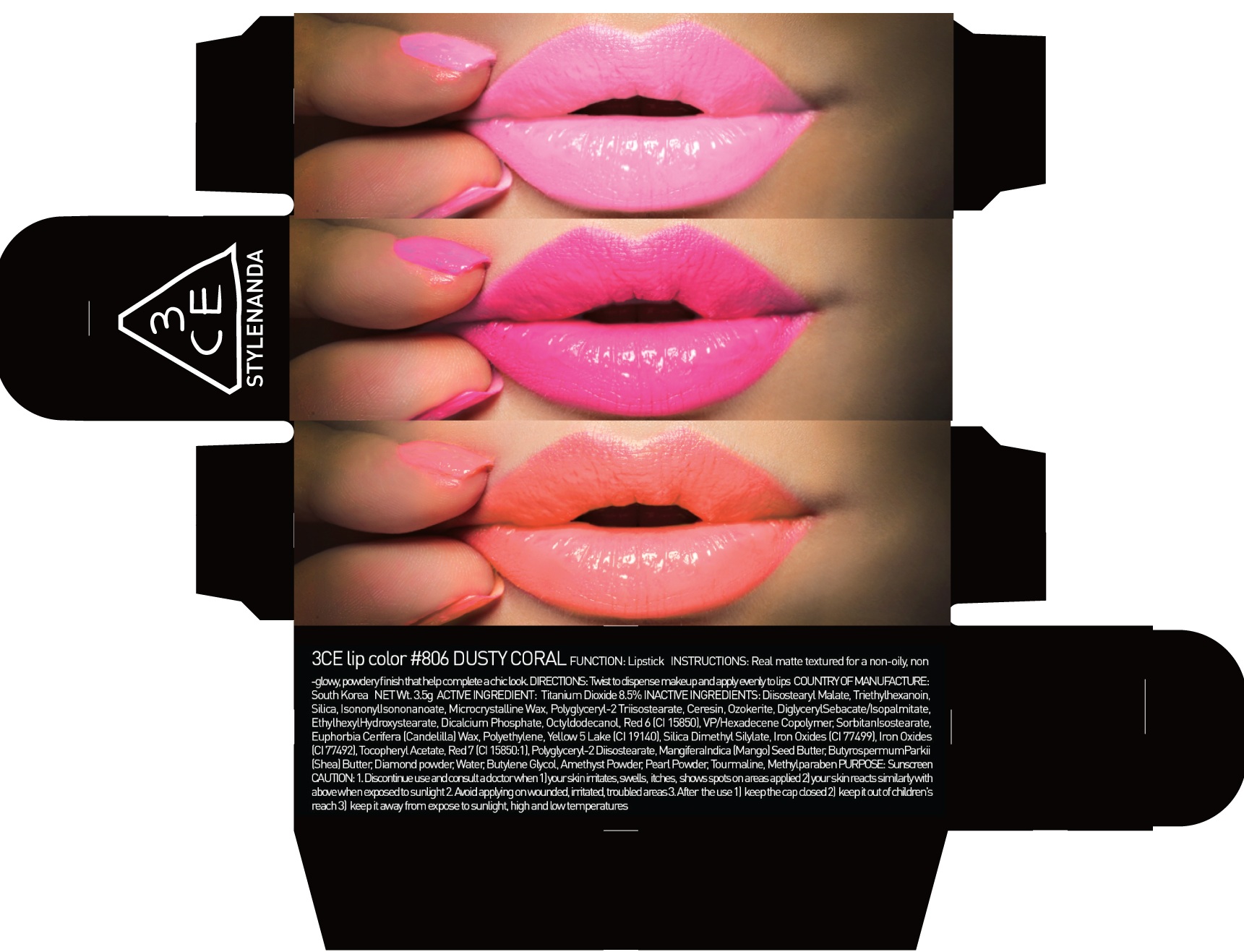 DRUG LABEL: 3CE LIP COLOR 806 DUSTY CORAL
NDC: 60764-052 | Form: LIPSTICK
Manufacturer: Nanda Co., Ltd
Category: otc | Type: HUMAN OTC DRUG LABEL
Date: 20160930

ACTIVE INGREDIENTS: Titanium Dioxide 0.29 g/3.5 g
INACTIVE INGREDIENTS: Diisostearyl Malate; Triethylhexanoin

ACTIVE INGREDIENT

Active Ingredient: Titanium Dioxide 8.5%

INACTIVE INGREDIENT

Inactive Ingredients: Diisostearyl Malate, Triethylhexanoin, Silica, IsononylIsononanoate, Microcrystalline Wax, Polyglyceryl-2 Triisostearate, Ceresin, Ozokerite, DiglycerylSebacate/Isopalmitate, EthylhexylHydroxystearate, Dicalcium Phosphate, Octyldodecanol, Red 6 (CI 15850), VP/Hexadecene Copolymer, SorbitanIsostearate, Euphorbia Cerifera (Candelilla) Wax, Polyethylene, Yellow 5 Lake (CI 19140), Silica Dimethyl Silylate, Iron Oxides (CI 77499), Iron Oxides (CI 77492), Tocopheryl Acetate, Red 7 (CI 15850:1), Polyglyceryl-2 Diisostearate, MangiferaIndica (Mango) Seed Butter, ButyrospermumParkii (Shea) Butter, Diamond powder, Water, Butylene Glycol, Amethyst Powder, Pearl Powder, Tourmaline, Methylparaben

PURPOSE

Purpose: Sunscreen

CAUTION

CAUTION: 1. Discontinue use and consult a doctor when - your skin irritates, swells, itches, shows spots on areas applied - your skin reacts similarly with above when exposed to sunlight 2. Avoid applying on wounded, irritated, troubled areas 3. After the use - keep the cap closed - keep it out of children's reach - keep it away from expose to sunlight, high and low temperatures

DESCRIPTION

INSTRUCTIONS: A rich color lipstick that moistly adheres to lips.

Directions: Twist to dispense makeup and apply evenly to lips